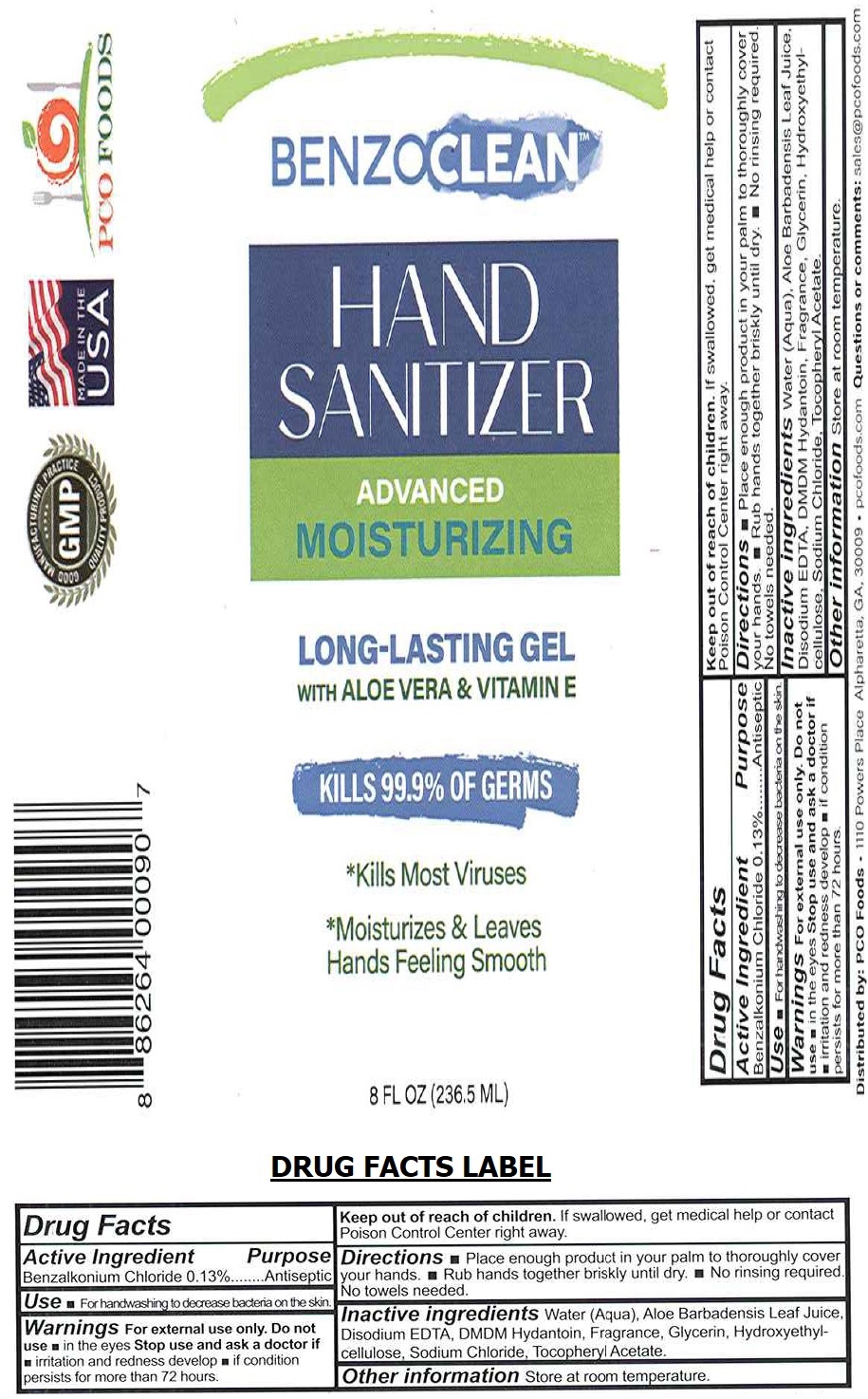 DRUG LABEL: BENZOCLEAN HAND SANITIZER
NDC: 53113-090 | Form: GEL
Manufacturer: GADAL Laboratories, Inc
Category: otc | Type: HUMAN OTC DRUG LABEL
Date: 20200711

ACTIVE INGREDIENTS: BENZALKONIUM CHLORIDE 0.13 g/100 mL
INACTIVE INGREDIENTS: WATER; ALOE VERA LEAF; EDETATE DISODIUM ANHYDROUS; DMDM HYDANTOIN; GLYCERIN; HYDROXYETHYL CELLULOSE, UNSPECIFIED; SODIUM CHLORIDE; .ALPHA.-TOCOPHEROL ACETATE

BENZOCLEANTM HAND SANITIZER

Active Ingredient

Benzalkonium Chloride 0.13%

Purpose

Antiseptic

INDICATIONS AND USAGE

Use ▪ For handwashing to decrease bacteria on the skin.

WARNINGS

Warnings For external use only. Do not use ▪ in the eyes Stop use and ask a doctor if ▪ irritation and redness develop ▪ if condition persists for more than 72 hours.

Keep out of reach of children. If swallowed, get medical help or contact Poison Control Center right away.

DOSAGE AND ADMINISTRATION

Directions ▪ Place enough product in your palm to thoroughly cover your hands. ▪ Rub hands together briskly until dry. ▪ No rinsing required. No towels needed.

Other information Store at room temperature.

INACTIVE INGREDIENT

Inactive ingredients Water (Aqua), Aloe Barbadensis Leaf Juice, Disodium EDTA, DMDM Hydantoin, Fragrance, Glycerin, Hydroxyethylcellulose, Sodium Chloride, Tocopheryl Acetate.

ADVANCED

MOISTURIZING

LONG-LASTING GEL

WITH ALOE VERA & VITAMIN E

KILLS 99.9% OF GERMS

*Kills Most Viruses

*Moisturizes & Leaves

Hands Feeling Smooth

MADE IN THE USA

GMP GOOD MANUFACTURING PRACTICE QUALITY PRODUCT

Distributed by: PCO Foods • 1110 Powers Place Alpharetta, GA, 30009 • pcofoods.com Questions or comments: sales@pcofoods.com